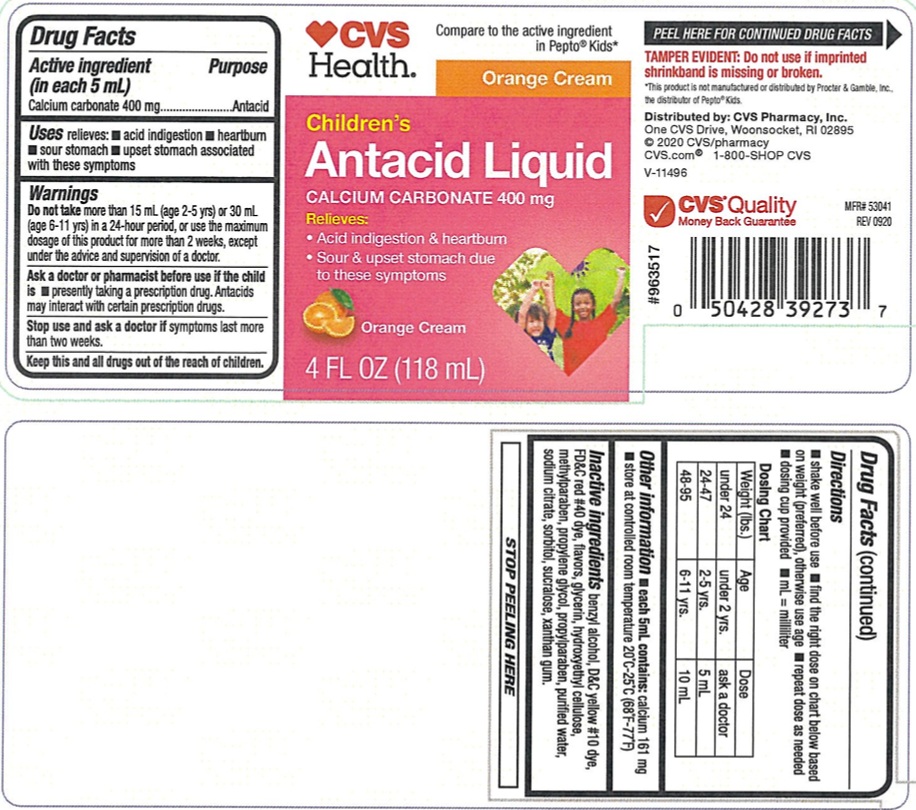 DRUG LABEL: Childrens Antacid
NDC: 51316-657 | Form: LIQUID
Manufacturer: CVS
Category: otc | Type: Human OTC Drug Label
Date: 20250116

ACTIVE INGREDIENTS: CALCIUM CARBONATE 400 mg/5 mL
INACTIVE INGREDIENTS: D&C YELLOW NO. 10; BENZYL ALCOHOL; FD&C RED NO. 40; GLYCERIN; HYDROXYETHYL CELLULOSE (2000 MPA.S AT 1%); METHYLPARABEN; PROPYLPARABEN; PROPYLENE GLYCOL; WATER; SODIUM CITRATE; SORBITOL; SUCRALOSE; XANTHAN GUM

Childrens Antacid Liquid

ACTIVE INGREDIENT (in each 5 mL)

Calcium carbonate 400 mg

PURPOSE

Antacid

USE(S)

relieves:

- acid indigestion
- heartburn
- sour stomach
- upset stomach associated with these symptoms

WARNINGS

Do not take nore than 15 mL (age 2-5 yrs) or 30 mL (age 6-11 yrs) in a 24-hour period, or use the maximum dosage of this product for more than 2 weeks, except under the advice and supervision of a doctor.

ASK A DOCTOR OR PHARMACIST BEFORE USE IF THE CHILD IS

- presently taking a prescription drug. Antacids may interact with certain prescription drugs.

STOP USE AND ASK DOCTOR IF

symptoms lasts more than two weeks

KEEP THIS AND ALL DRUGS OUT OF REACH OF CHILDREN

.

DIRECTIONS

- shake well before use
- find the right dose on the chart below based on weight (preferred), otherwise use age.
- repeat dose as needed
- dosing cup provided
- mL=milliliter

Dosing Chart

Weight (lbs.) | Age | Dose
under 24 | under 2 yrs. | ask a doctor
24-47 | 2-5 yrs. | 5 mL
48-95 | 6-11 yrs. | 10 mL

OTHER INFORMATION

- each 5 mL contains: calcium 161 mg
- store at controlled room temperature 20-25ºC (68ºF-77ºF)

INACTIVE INGREDIENTS

benzyl alcohol, D&C yellow#10 dye, FD&C red#40 dye, flavors, glycerin, hydroxyethyl cellulose, methylparaben, propylene glycol, propylparaben, purified water, sodium citrate, sorbitol, sucralose, xanthan gum.

PRINCIPAL DISPLAY PANEL

CVS

Health.

Compare to the active ingredient in pepto® kids*

Orange Cream
NDC 51316-657-03
Children's
Antacid Liquid

CALCIUM CARBONATE 400 mg

RELIEVES :

- Acid indigestion & heartburn
- Sour & upset Stomach due to these symptoms

Orange Cream
4 FL OZ (118 mL)